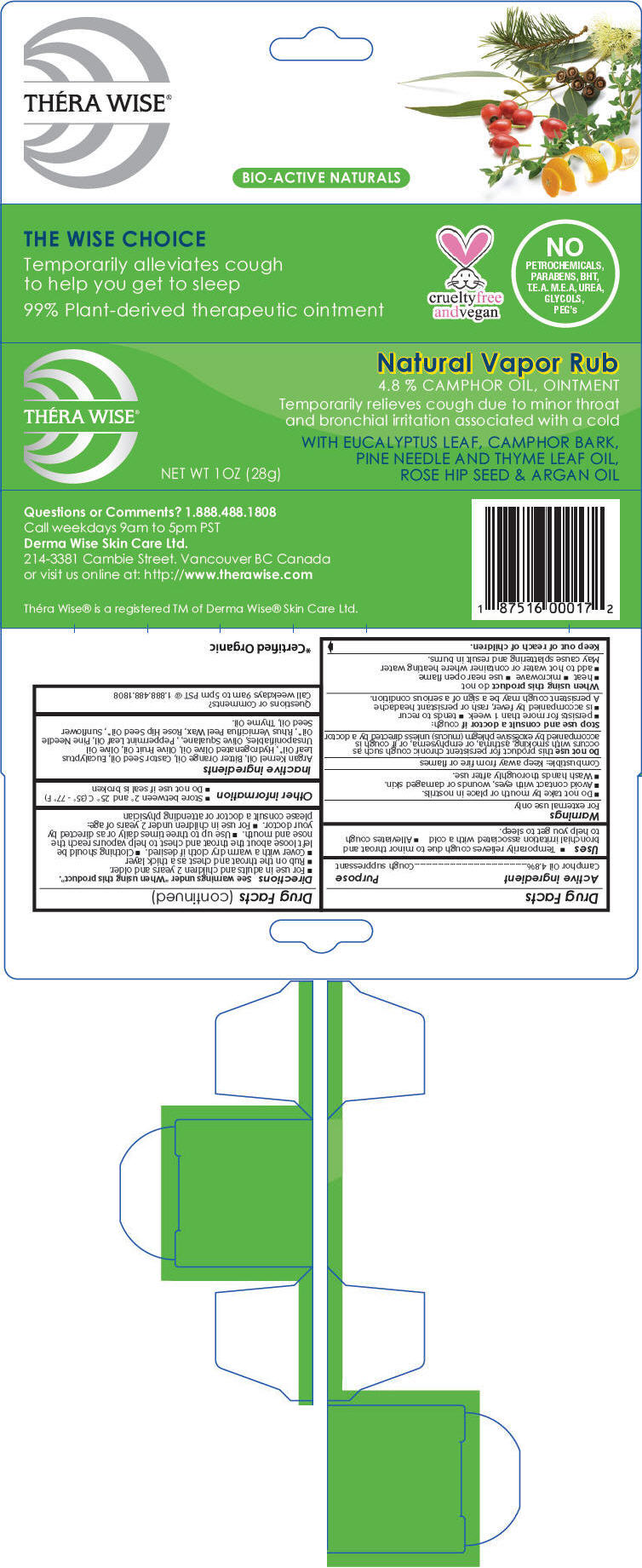 DRUG LABEL: Thera Wise Natural Vapor Rub
NDC: 43347-172 | Form: OINTMENT
Manufacturer: Derma Wise Skin Care Ltd.
Category: otc | Type: HUMAN OTC DRUG LABEL
Date: 20160719

ACTIVE INGREDIENTS: CAMPHOR (NATURAL) 1.344 g/28 g
INACTIVE INGREDIENTS: Argan Oil; Bitter Orange Oil; Castor Oil; Eucalyptus Oil; Hydrogenated Olive Oil; Olive Oil; Olea Europaea (Olive) Oil Unsaponifiables; Squalane; Mentha Piperita Leaf; Pine Needle Oil (Pinus Sylvestris); Toxicodendron Vernicifluum Fruit Rind Wax; Rosa Moschata Oil; Sunflower Oil; Thyme Oil

Théra Wise® Natural Vapor Rub

Drug Facts

Active ingredient

Camphor Oil 4.8%

Purpose

Cough suppressant

Uses

- Temporarily relieves cough due to minor throat and bronchial irritation associated with a cold
- Alleviates cough to help you get to sleep.

Warnings

For external use only

- Do not take by mouth or place in nostrils.
- Avoid contact with eyes, wounds or damaged skin.
- Wash hands thoroughly after use.

Combustible: Keep away from fire or flames

Do not use this product for persistent chronic cough such as occurs with smoking, asthma, or emphysema, or if cough is accompanied by excessive phlegm (mucus) unless directed by a doctor

Stop use and consult a doctor if cough:

- persists for more than 1 week
- tends to recur
- is accompanied by fever, rash or persistant headache

A persistent cough may be a sign of a serious condition.

When using this product do not

- heat
- microwave
- use near open flame
- add to hot water or container where heating water

May cause splattering and result in burns.

Keep out of reach of children.

Directions

See warnings under "When using this product".

- For use in adults and children 2 years and older.
- Rub on the throat and chest as a thick layer
- Cover with a warm dry cloth if desired.
- Clothing should be left loose about the throat and chest to help vapours reach the nose and mouth.
- Use up to three times daily or as directed by your doctor.
- For use in children under 2 years of age: please consult a doctor or attending physician

Other information

- Store between 2° and 25° C (35° - 77° F)
- Do not use if seal is broken

Inactive ingredients

Argan Kernel Oil, Bitter Orange Oil, Castor Seed Oil, Eucalyptus Leaf Oil [Certified Organic] , Hydrogenated Olive Oil, Olive Fruit Oil, Olive Oil Unsaponifiables, Olive Squalane, , Peppermint Leaf Oil, Pine Needle Oil, Rhus Verniciflua Peel Wax, Rose Hip Seed Oil, Sunflower Seed Oil, Thyme Oil.

Questions or Comments?

Call weekdays 9am to 5pm PST @ 1.888.488.1808

PRINCIPAL DISPLAY PANEL - 28 g Tube Box

THÉRA WISE®

Natural Vapor Rub
4.8 % CAMPHOR OIL, OINTMENT

Temporarily relieves cough due to minor throat
and bronchial irritation associated with a cold

WITH EUCALYPTUS LEAF, CAMPHOR BARK,
PINE NEEDLE AND THYME LEAF OIL,
ROSE HIP SEED & ARGAN OIL

NET WT 1OZ (28g)